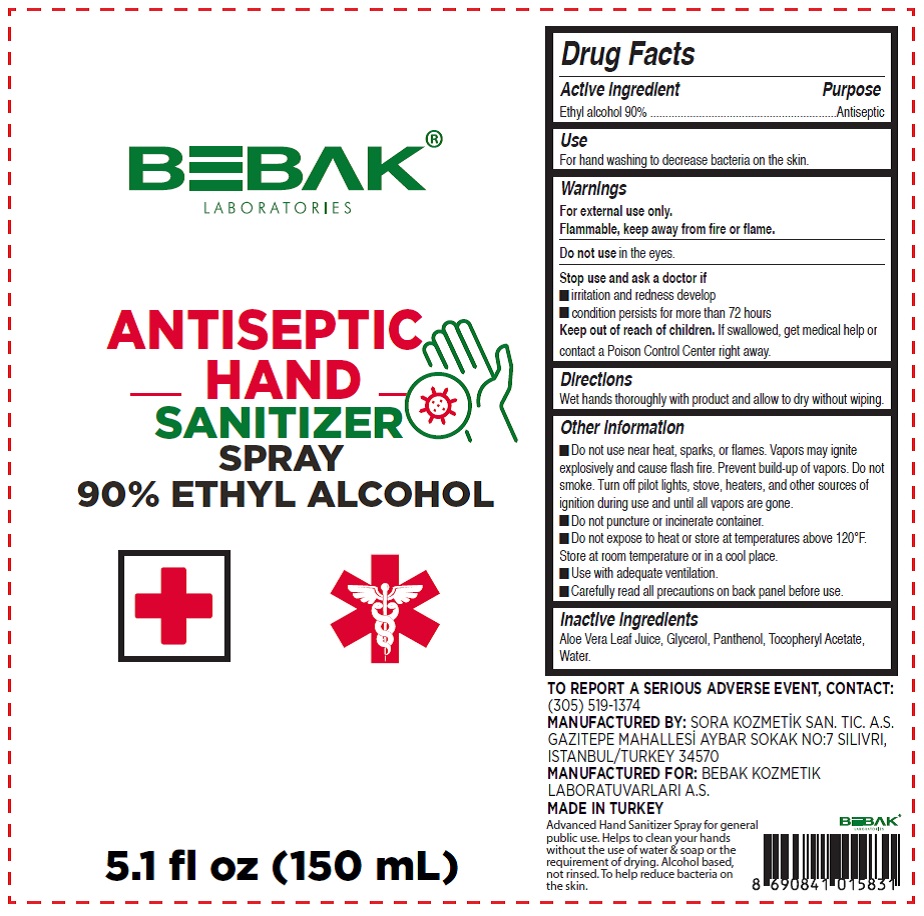 DRUG LABEL: Bebak Laboratories Hand Sanitizer
NDC: 77462-003 | Form: AEROSOL
Manufacturer: SORA KOZMETIK SANAYI TICARET ANONIM SIRKETI
Category: otc | Type: HUMAN OTC DRUG LABEL
Date: 20200618

ACTIVE INGREDIENTS: ALCOHOL 90.24 mL/100 mL
INACTIVE INGREDIENTS: ALOE VERA LEAF; PANTHENOL; WATER; GLYCERIN; ALPHA-TOCOPHEROL ACETATE

Bebak Laboratories

Active Ingredient

Ethyl alcohol 90%

Purpose

Antiseptic

Use

For hand washing to decrease bacteria on the skin.

Warnings

For external use only.

Flammable, keep away from fire or flame.

Do not use in the eyes.

Stop use and ask a doctor if

- irritation and redness develop
- condition persist for more than 72 hours

Keep out of reach of children. If swallowed, get medical help or contact a Poison Control Center right away.

Directions

Wet hands thoroughly with product and allow to dry without wiping.

Other information

- Do not use near heat, sparks, or flames. Vapors may ignite explosively and cause flash fire. Prevent build-up of vapors. Do not smoke. Turn off pilot lights, stove, heaters, and other sources of ignition during use and until all vapors are gone.
- Do not puncture or incinerate container.
- Do not expose to heat or store at temperatures above 120F. Store at room temperature or in a cool place.
- Use with adequate ventilation.
- Carefully read all precautions on back panel before use.

Inactive ingredients

Aloe Vera Juice, Glycerol, Panthenol, Tocopheryl Acetate, Water.